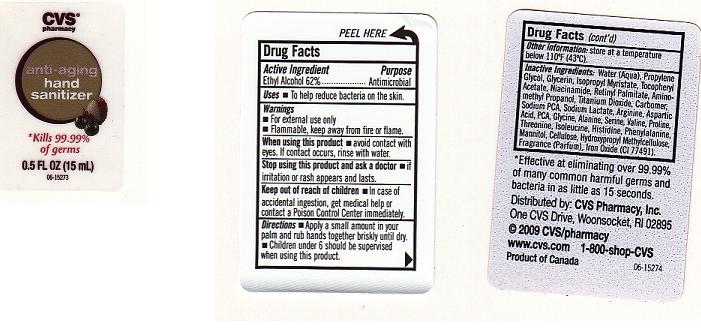 DRUG LABEL: ANTI-AGING HAND SANITIZER
NDC: 59779-251 | Form: GEL
Manufacturer: CVS PHARMACY
Category: otc | Type: HUMAN OTC DRUG LABEL
Date: 20110318

ACTIVE INGREDIENTS: ALCOHOL 62 mL/100 mL
INACTIVE INGREDIENTS: WATER; PROPYLENE GLYCOL; GLYCERIN; ISOPROPYL MYRISTATE; ALPHA-TOCOPHEROL ACETATE; NIACINAMIDE; VITAMIN A PALMITATE; AMINOMETHYLPROPANOL; TITANIUM DIOXIDE; CARBOMER HOMOPOLYMER TYPE C; SODIUM PYRROLIDONE CARBOXYLATE; SODIUM LACTATE; ARGININE; ASPARTIC ACID; GLYCINE; ALANINE; SERINE; VALINE; PROLINE; THREONINE; ISOLEUCINE; HISTIDINE; PHENYLALANINE; MANNITOL; POWDERED CELLULOSE; HYPROMELLOSES; FERRIC OXIDE RED

DRUG FACTS

ACTIVE INGREDIENT

ETHYL ALCOHOL 62%

PURPOSE

ANTIMICROBIAL

USES

TO HELP REDUCE BACTERIA ON THE SKIN.

WARNINGS

FOR EXTERNAL USE ONLY.

FLAMMABLE, KEEP AWAY FROM FIRE OR FLAME.

WHEN USING THIS PRODUCT

AVOID CONTACT WITH EYES. IF CONTACT OCCURS, RINSE WITH WATER.

STOP USING THIS PRODUCT AND ASK A DOCTOR

IF IRRITATION OR RASH APPEARS AND LASTS.

KEEP OUT OF REACH OF CHILDREN

IN CASE OF ACCIDENTAL INGESTION, GET MEDICAL HELP OR CONTACT A POISON CONTROL CENTER IMMEDIATELY.

DIRECTIONS

APPLY A SMALL AMOUNT IN YOUR PALM AND RUB HANDS TOGETHER BRISKLY UNTIL DRY. CHILDREN UNDER 6 SHOULD BE SUPERVISED WHEN USING THIS PRODUCT.

OTHER INFORMATION

STORE AT A TEMPERATURE BELOW 110 DEGREES FAHRENHEIT(43 DEGREES CELSIUS).

INACTIVE INGREDIENTS

WATER, PROPYLENE GLYCOL, GLYCERIN, ISOPROPYL MYRISTATE, TOCOPHERYL ACETATE, NIACINAMIDE, RETINYL PALMITATE, AMINOMETHYL PROPANOL, TITANIUM DIOXIDE, CARBOMER, SODIUM PCA, SODIUM LACTATE, ARGININE, ASPARTIC ACID, PCA, GLYCINE, ALANINE, SERINE, VALINE, PROLINE, THREONINE, ISOLEUCINE, HISTIDINE, PHENYLALANINE, MANNITOL, CELLULOSE, HYDROXYPROPYL METHYLCELLULOSE, FRAGRANCE, IRON OXIDE (CI 77491).